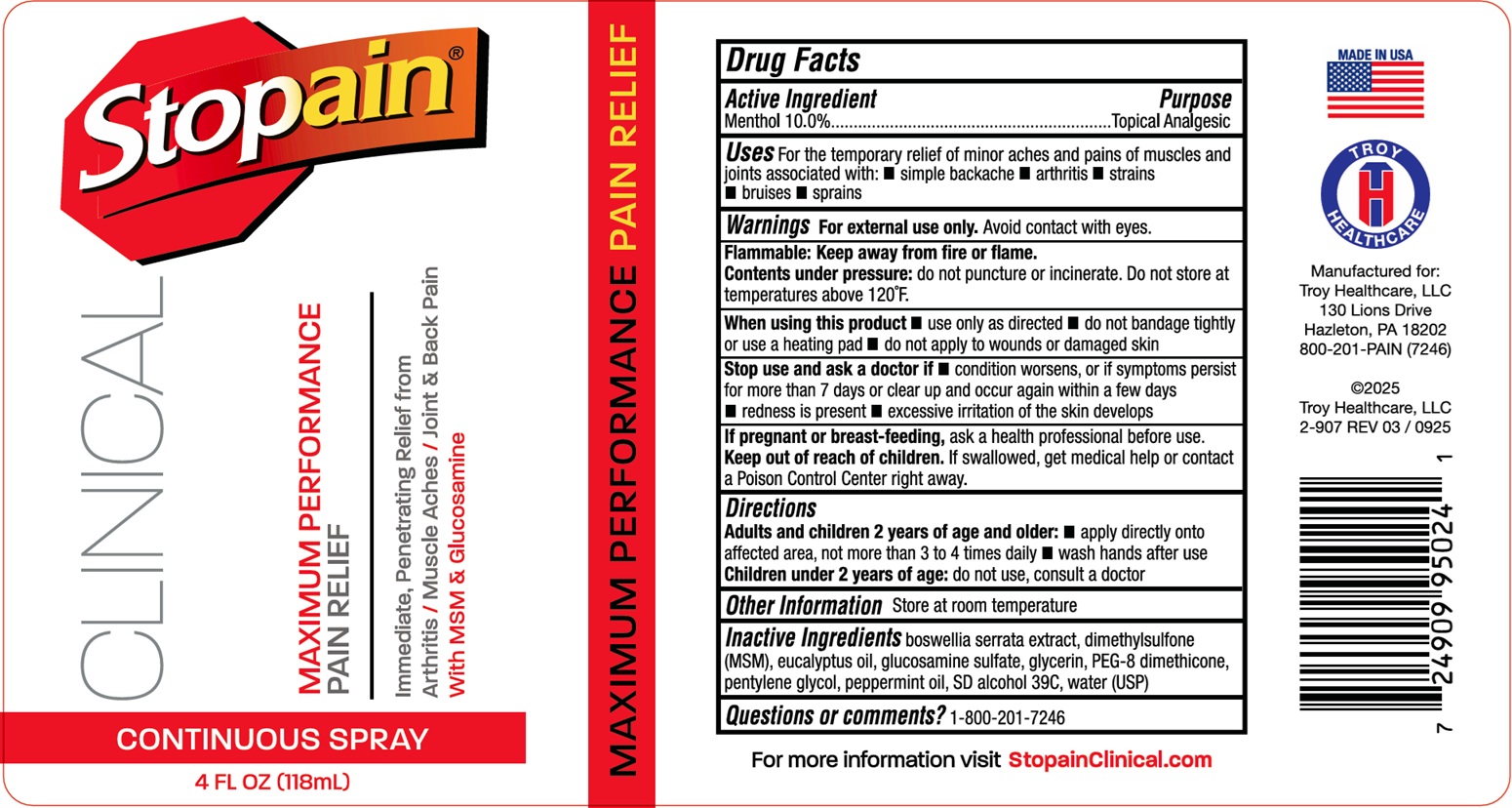 DRUG LABEL: Stopain Clinical Continuous
NDC: 63936-9504 | Form: LIQUID
Manufacturer: Troy Manufacturing, Inc.
Category: otc | Type: HUMAN OTC DRUG LABEL
Date: 20251209

ACTIVE INGREDIENTS: MENTHOL 100 mg/1 mL
INACTIVE INGREDIENTS: INDIAN FRANKINCENSE; DIMETHYL SULFONE; EUCALYPTUS OIL; GLUCOSAMINE SULFATE; GLYCERIN; PEG-8 DIMETHICONE; PENTYLENE GLYCOL; PEPPERMINT OIL; WATER

Stopain Clinical Continuous Spray

Active Ingredient

Menthol 10.0%

Purpose

Topical Analgesic

Uses

For the temporary relief of minor aches and pains of muscles and joints associated with:

- simple backache
- arthritis
- strains
- bruises
- sprains

Warnings

For external use only. Avoid contact with eyes.

Flammable: Keep away from fire or flame.

Contents under pressure: do not puncture or incinerate. Do not store at temperature above 120°F.

When using this product:

- use only as directed
- do not bandage tightly or use a heating pad
- do not apply to wounds or damaged skin

Stop use and ask a doctor if

- condition worsens or if symptoms persist for more than 7 days or clear up and occur again within a few days
- redness is present
- excessive irritation of the skin develops

If pregnant or breast-feeding,

ask a health prefessional before use.

Keep out of reach of children.

If swallowed, get medical help or contact a Poison Control Center right away.

Directions

Adults and children over 12 years:

- apply directly onto affected area without the need to rub, massage or bandage
- repeat if necessary, but do not apply more than 4 times daily.

Children 12 years or younger: ask a doctor.

Other Information

- Store at room temperature.

Inactive Ingredients

boswellia serrata extract, dimethylsulfone (MSM), eucalyptus oil, glucosamine sulfate, glycerine, PEG-8 dimethicone, pentylene glycol, peppermint oil, SD alcohol 39C, water (USP).